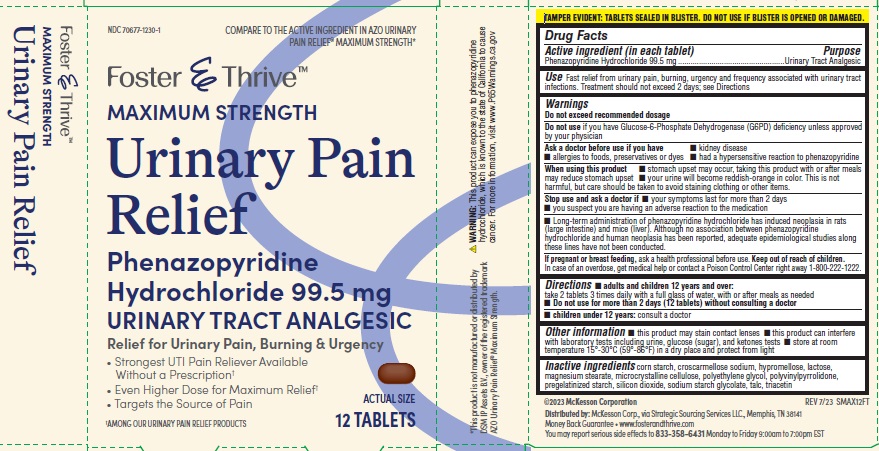 DRUG LABEL: Foster and Thrive Maximum Strength Urinary Pain Relief
NDC: 70677-1230 | Form: TABLET
Manufacturer: Strategic Sourcing Services LLC
Category: otc | Type: HUMAN OTC DRUG LABEL
Date: 20240621

ACTIVE INGREDIENTS: PHENAZOPYRIDINE HYDROCHLORIDE 99.5 mg/1 1
INACTIVE INGREDIENTS: LACTOSE; STARCH, CORN; CROSCARMELLOSE SODIUM; HYPROMELLOSE, UNSPECIFIED; MAGNESIUM STEARATE; MICROCRYSTALLINE CELLULOSE; POLYETHYLENE GLYCOL, UNSPECIFIED; POVIDONE, UNSPECIFIED; SILICON DIOXIDE; SODIUM STARCH GLYCOLATE TYPE A CORN; TALC; TRIACETIN

DRUG FACTS

Active ingredient (in each tablet)

Phenazopyridine Hydrochloride 99.5 mg .

Purpose

Urinary Analgesic

Warnings

Do not exceed recommended dosage

Do not use if you have Glucose-6-Phosphate Dehydrogenase (G6PD) deficiency unless approved by your physician

Ask doctor before use if you have

■ kidney disease
■ allergies to food, preservatives or dyes
■ had a hypersensitive reaction to phenazopyridine

When using this product

■ stomach upset may occur, taking this product with or after meals may
reduce stomach upset
■ your urine will become reddish-orange in color. This is not harmful, but
care should be taken to avoid staining clothing or other items.

Stop use and ask doctor if

■ your symptoms last for more than 2 days
■ you suspect you are having an adverse reaction to the medication

Long-term administration of phenazopyridine hydrochloride has induced neoplasia in rats (large intestine) and mice (liver). Although no association between phenazopyridine hydrochloride and human neoplasia has been reported, adequate epidemiological studies along these lines have not been conducted.

If pregnant or breast feeding,

Ask a health professional before use.

Keep out of reach of children

In case of an overdose, get medical help or contact a Poison Control Center right away.

Use

Fast relief from urinary pain, burning, urgency and frequency associated with urinary tract
infections.

Inactive ingredients

corn starch, croscarmellose sodium, hypromellose, lactose, magnesium stearate, microcrystalline cellulose, polyethylene glycol, polyvinylpyrrolidone, pregelatinized starch, silicon dioxide, sodium starch glycolate, talc and triacetin

Directions

■ adults and children 12 years and over:
take 2 tablets 3 times daily with a full glass of water, with or after meals as needed

■ children under 12 years: consult a doctor

■ Do not use for more than 2 days (12 tablets) without consulting a doctor